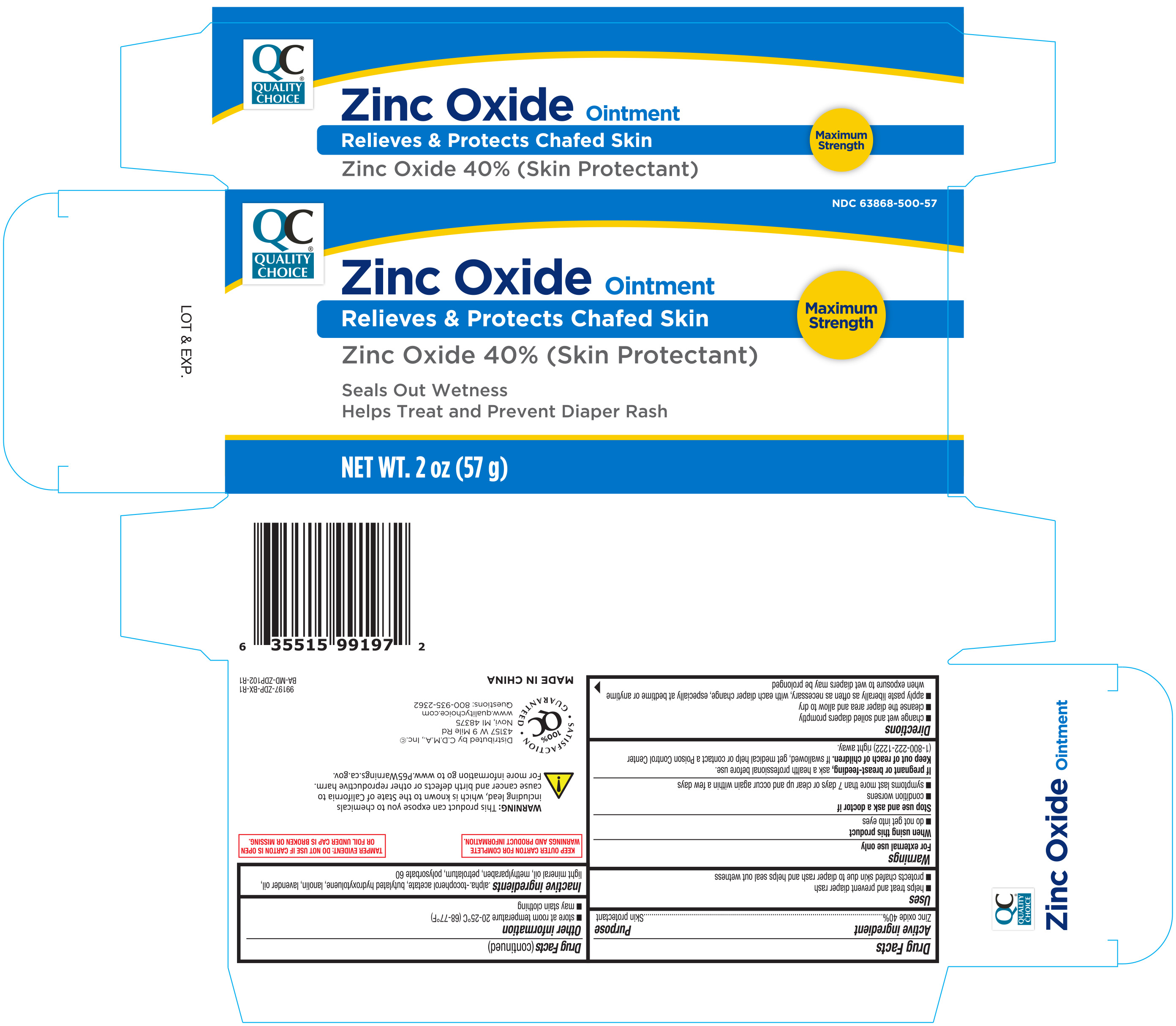 DRUG LABEL: Quality Choice Maximum Strength Zinc Oxide
NDC: 63868-500 | Form: OINTMENT
Manufacturer: Chain Drug Marketing Association Inc
Category: otc | Type: HUMAN OTC DRUG LABEL
Date: 20221216

ACTIVE INGREDIENTS: ZINC OXIDE 40 g/100 g
INACTIVE INGREDIENTS: .ALPHA.-TOCOPHEROL ACETATE; LAVENDER OIL; BUTYLATED HYDROXYTOLUENE; POLYSORBATE 60; LANOLIN; METHYLPARABEN; PETROLATUM; LIGHT MINERAL OIL

QC Zinc Oxide Ointment 2 oz 99197 ZDP

Active ingredient

Zinc oxide 40%...........................Skin protectant

Uses

- helps treat and prevent diaper rash
- protects chafed skin due to diaper rash and helps seal out wetness

Warnings

For external use only

When using this product

- do not get into eyes

Stop use and ask a doctor if

- condition worsens
- symptoms last more than 7 days or clear up and occur again within a few days

If pregnant or breast-feeding

ask a health professional before use.

Keep out of reach of children

If swallowed, get medical help or contact a Poison Control Center (1-800-222-1222) right away.

Directions

- change wet and soiled diapers promptly
- cleanse the diaper area, and allow to dry
- apply paste liberally as often as necessary, with each diaper change, especially at bedtime or anytime exposure to wet diapers may be prolonged

Other information

- store at 20°-25°C (68°-77°F)
- may stain clothing

Inactive ingredients

.alpha.-tocopherol acetate, butylated hydroxytoluene, lanolin, lavender oil, light mineral oil, methylparaben, petrolatum, polysorbate 60

DOSAGE AND ADMINISTRATION

DISTRIBUTED BY:

C.D.M.A., INC.

43157 W. NINE MILE

NOVI, MI 48376

www.qualitychoice.com

Made in China